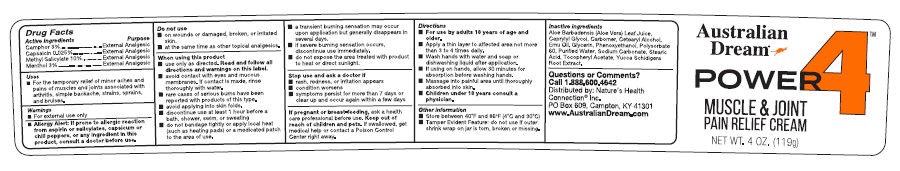 DRUG LABEL: Australian Dream Power 4 Muscle and Joint Pain Relief Cream
NDC: 61577-8220 | Form: CREAM
Manufacturer: Sombra Cosmetics, Inc.
Category: otc | Type: HUMAN OTC DRUG LABEL
Date: 20230510

ACTIVE INGREDIENTS: METHYL SALICYLATE 0.10 g/1 g; MENTHOL 0.03 g/1 g; CAMPHOR (SYNTHETIC) 0.03 g/1 g; CAPSAICIN 0.025 g/1 g
INACTIVE INGREDIENTS: WATER; CARBOMER COPOLYMER TYPE A; TOCOPHEROL; CETOSTEARYL ALCOHOL; POLYSORBATE 60; STEARIC ACID; EMU OIL; GLYCERIN; PHENOXYETHANOL; CAPRYLYL GLYCOL; YUCCA SCHIDIGERA ROOT; ALOE VERA LEAF; SODIUM CARBONATE

Australian Dream Power 4 Muscle & Joint Pain Relief Cream

Active Ingredients

Camphor 3%, Capsaicin 0.025%, Methyl Salicylate 10%, Menthol 3%

Keep out of reach of children and pets.

If swallowed, get medical help or contact a Poison Control Center right away

PURPOSE

Topical Analgesic

Uses

For temporary relief of minor aches and pains of muscles and joints associated with arthritis, simple backache, strains, sprains, and bruises.

Warnings

For external use only. Allery Alert: If prone to allergic reaction from asprin or salicylates, capsisum or chili peppers, or any ingredients in this product, consult a doctor before use. Do not use on wounds or damaged, broken, or irritated skin, at the same time as other topical analgesics. When using this product, use only as directed. Read and follow all directions and warning on this label. Aviod contact with eyes and mucous membranes. If contact is made, rinse thoroughly with water. Rare cases of serious burns have been reported with this type of product. Avoid applying into skin folds. Discontinue use at leat 1 hour before a bath, shower, swim, or sweating. Do not bandage tightly or apply local heat (such as heating pads) or a medicated patch to the area of use. A transient burning sensation may occur upon application but generlly disappears in several days. If severe burning sensation occurs, discontinue use immediately. Do notexpoes the area treated with product to heat or direct sunlight. Stop use and ask a doctor if, rash, redness or irritation appears, condition worsens, symtoms persist for more than 7 days or clear up and occur again within a few days. If pregnant or breast-feeding, ask a health care professional before use.

Directions

For use by adults 18 years of age and older. Apply a thin layer to affected area not more than 3 to 4 times daily. Wash hands with soap or dishwashing liquid after application. If using on hands, allow 30 minutes for absorption before washing hands. Massage intopainful area until thoroughly absorbed into skin. Children under 18 years consult a physician. Store between 40F and 86F (4C and 30C), Tamper Evident Feature: do not use if outer shrink wrap on jar is torn, broken or missing.

Inactive Ingredients

Aloe Barbadensis (Aloe Vera) Leaf Juice, Caprylyl Glycol, Carbomer, Cetearyl Alcohol, Emu Oil, Glycerin, Phenoxyethanol, Polysorbate 60, Purifed Water, Sodium Carbonate, Stearic Acid, Tocopheryl Acetate, Yucca Schidigera Root Extract.

Questions or Comments?

Call 1-888-600-4642